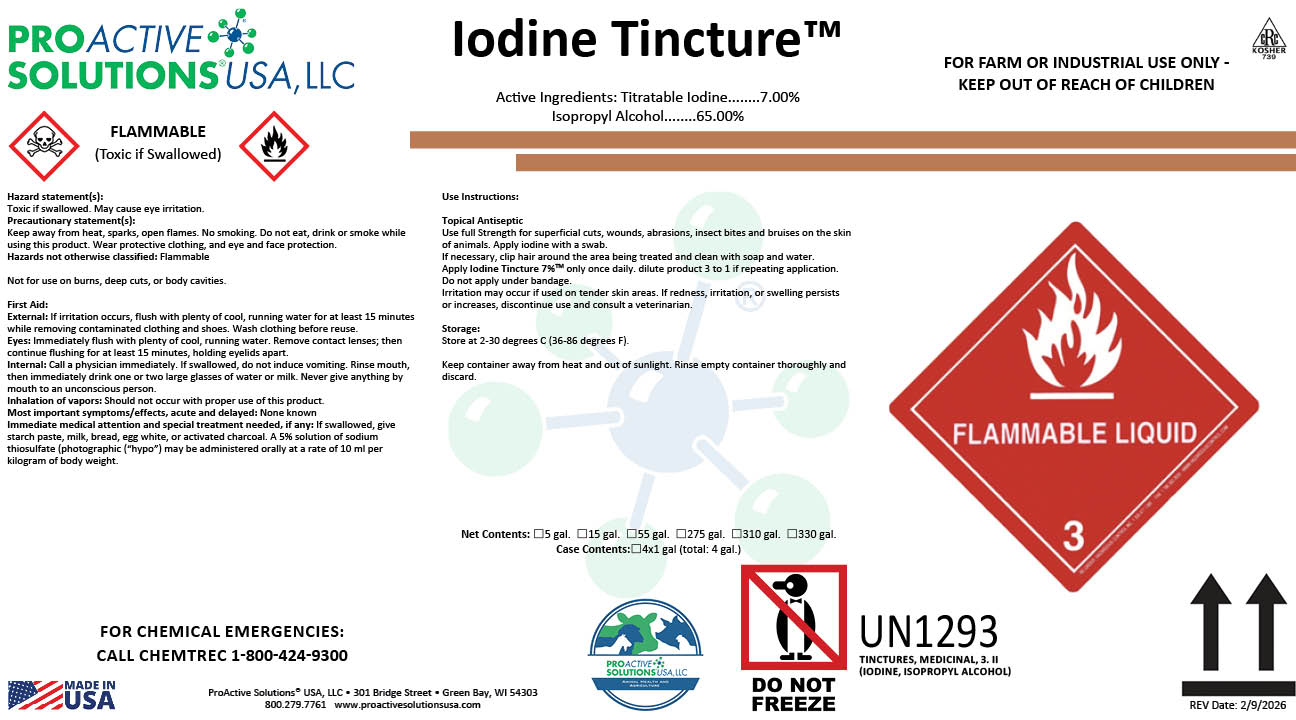 DRUG LABEL: Iodine Tincture 7%
NDC: 63927-4240 | Form: LIQUID
Manufacturer: ProActive Solutions USA, LLC
Category: animal | Type: OTC ANIMAL DRUG LABEL
Date: 20260210

ACTIVE INGREDIENTS: IODINE 7 kg/100 kg; ISOPROPYL ALCOHOL 65 kg/100 kg

Iodine Tincture 7%

Iodine Tincture 7%

Use Instructions:
Topical Antiseptic
Use full Strength for superficial cuts, wounds, abrasions, insect bites and bruises on the skin
of animals. Apply iodine with a swab.
If necessary, clip hair around the area being treated and clean with soap and water.
Apply Iodine Tincture 7%TM only once daily. dilute product 3 to 1 if repeating application.
Do not apply under bandage.
Irritation may occur if used on tender skin areas. If redness, irritation, or swelling persists
or increases, discontinue use and consult a veterinarian.
Storage:
Store at 2-30 degrees C (36-86 degrees F).
Keep container away from heat and out of sunlight. Rinse empty container thoroughly and
discard.

Hazard statement(s):
Toxic if swallowed. May cause eye irritation.
Precautionary statement(s):
Keep away from heat, sparks, open flames. No smoking. Do not eat, drink or smoke while
using this product. Wear protective clothing, and eye and face protection.
Hazards not otherwise classified: Flammable
Not for use on burns, deep cuts, or body cavities.
First Aid:
External: If irritation occurs, flush with plenty of cool, running water for at least 15 minutes
while removing contaminated clothing and shoes. Wash clothing before reuse.
Eyes: Immediately flush with plenty of cool, running water. Remove contact lenses; then
continue flushing for at least 15 minutes, holding eyelids apart.
Internal: Call a physician immediately. If swallowed, do not induce vomiting. Rinse mouth,
then immediately drink one or two large glasses of water or milk. Never give anything by
mouth to an unconscious person.
Inhalation of vapors: Should not occur with proper use of this product.
Most important symptoms/effects, acute and delayed: None known
Immediate medical attention and special treatment needed, if any: If swallowed, give
starch paste, milk, bread, egg white, or activated charcoal. A 5% solution of sodium
thiosulfate (photographic (“hypo”) may be administered orally at a rate of 10 ml per
kilogram of body weight.